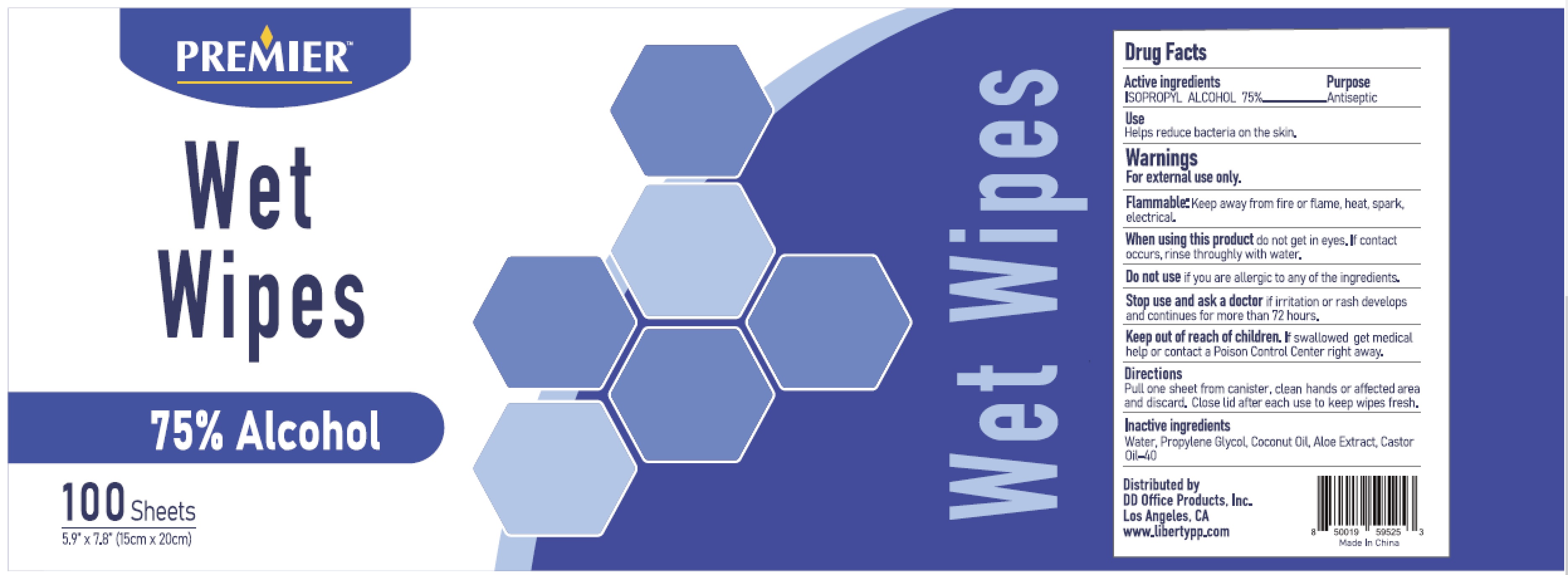 DRUG LABEL: PREMIER Wet Wipes
NDC: 77081-100 | Form: CLOTH
Manufacturer: D D Office Products, Inc.
Category: otc | Type: HUMAN OTC DRUG LABEL
Date: 20200812

ACTIVE INGREDIENTS: ISOPROPYL ALCOHOL 0.75 1/1 1
INACTIVE INGREDIENTS: PROPYLENE GLYCOL; COCONUT OIL; WATER; ALOE VERA LEAF; CASTOR OIL

PREMIER Wet Wipes

Active Ingredients

ISOPROPYL ALCOHOL 75%

Purpose

Antiseptic

Use

Helps reduce bacteria on the skin.

Warnings

For external use only. Flammable.Keep away from fire or flame, heat, spark, electrical.

When using this product do not get in eyes. If contact occurs,rise throughly with water.

Do not use

if you are allergic to any of the ingredients.

Stop use and ask a doctor if irritation or rash develops and continues for more than 72 hours.

Keep out of reach of children. If swallowed, get medical help or contact a Poison Control Center right away.

Directions

Pull one sheet from canister, clean hands or affected area and discard. Close lid after each use to keep wipes fresh.

Inactive ingredients

Water, Propylene Glycol, Coconut Oil, Aloe Extract, Castor Oil-40